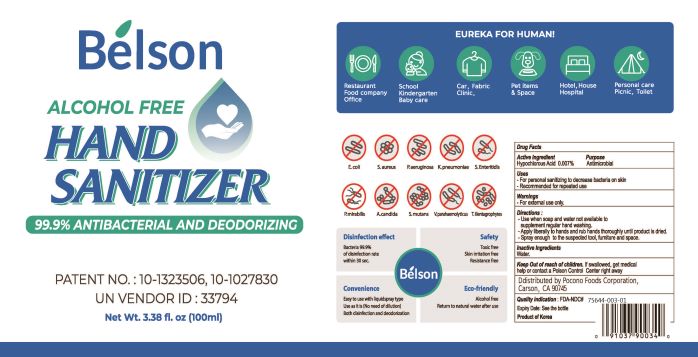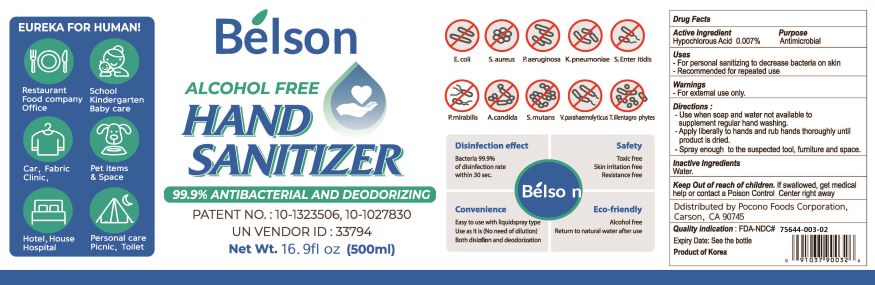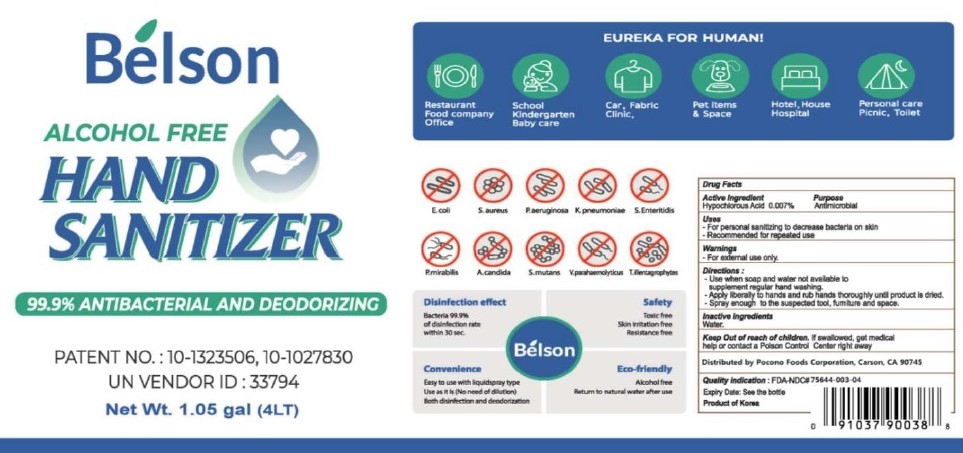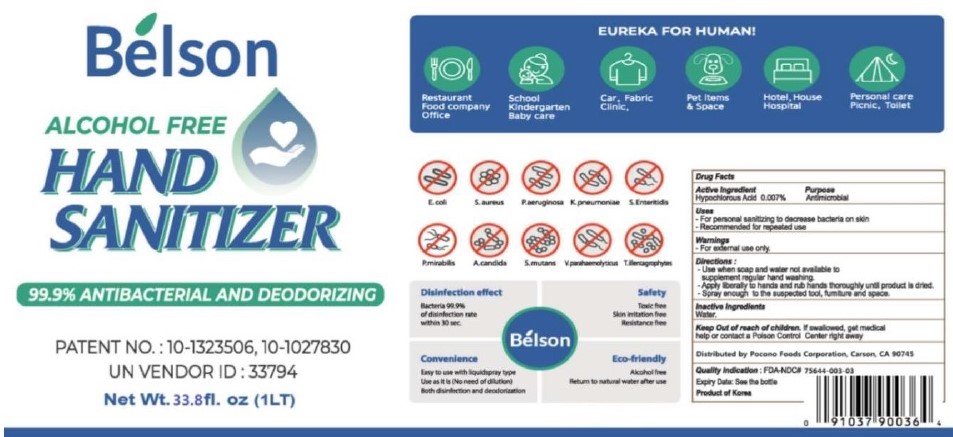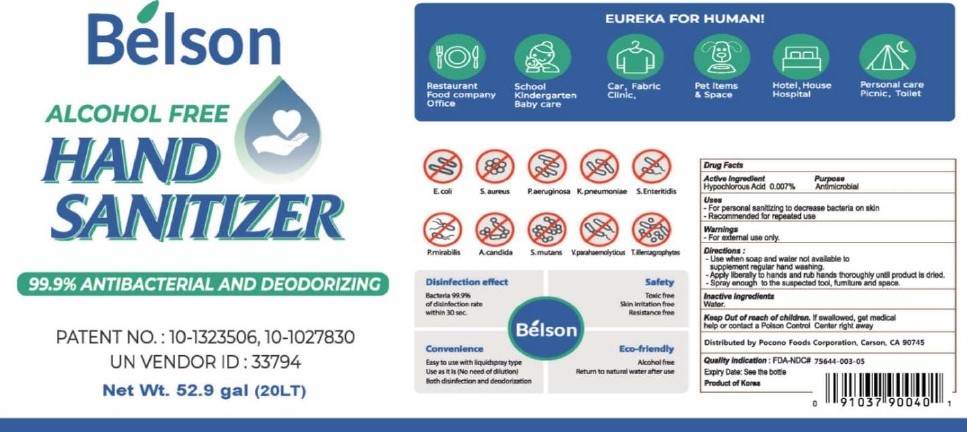 DRUG LABEL: BELSON ALCOHOL FREE HAND SANIZITER
NDC: 75644-003 | Form: LIQUID
Manufacturer: KEWS CORPORATION
Category: otc | Type: HUMAN OTC DRUG LABEL
Date: 20220118

ACTIVE INGREDIENTS: HYPOCHLOROUS ACID 0.007 mg/1 mL
INACTIVE INGREDIENTS: WATER

BELSON ALCOHOL FREE HAND SANITIZER

ACTIVE INGREDIENT

HYPOCHLOROUS ACID -- 0.007%

Inactive Ingredients

Water

Purpose

Antimicrobial

Directions for Use

-Use when soap and water not available to supplement regular hand washing.

-Apply liberally to hands and rub hands thorougly until product is dried

-Spray enough to the suspected tool, furniture and space.

Intended Use

-For personal sanitizing to decrease bacteria on skin

-Recommended for repeated use

USES

-For personal sanitzing to decrease bacteria on skin

-Recommended for repeated use

Keep out of reach of children.

If swallowed, get medical help or contact a Poison Control Center right away.

Warnings

For External Use

100mL PDP

100mL NDC 75644-003-01

500mL PDP

500mL NDC 75644-003-02

1LT PDP

1LT NDC 75644-003-03

4LT PDP

4LT NDC 75644-003-04

20LT PDP

20LT NDC 75644-003-05